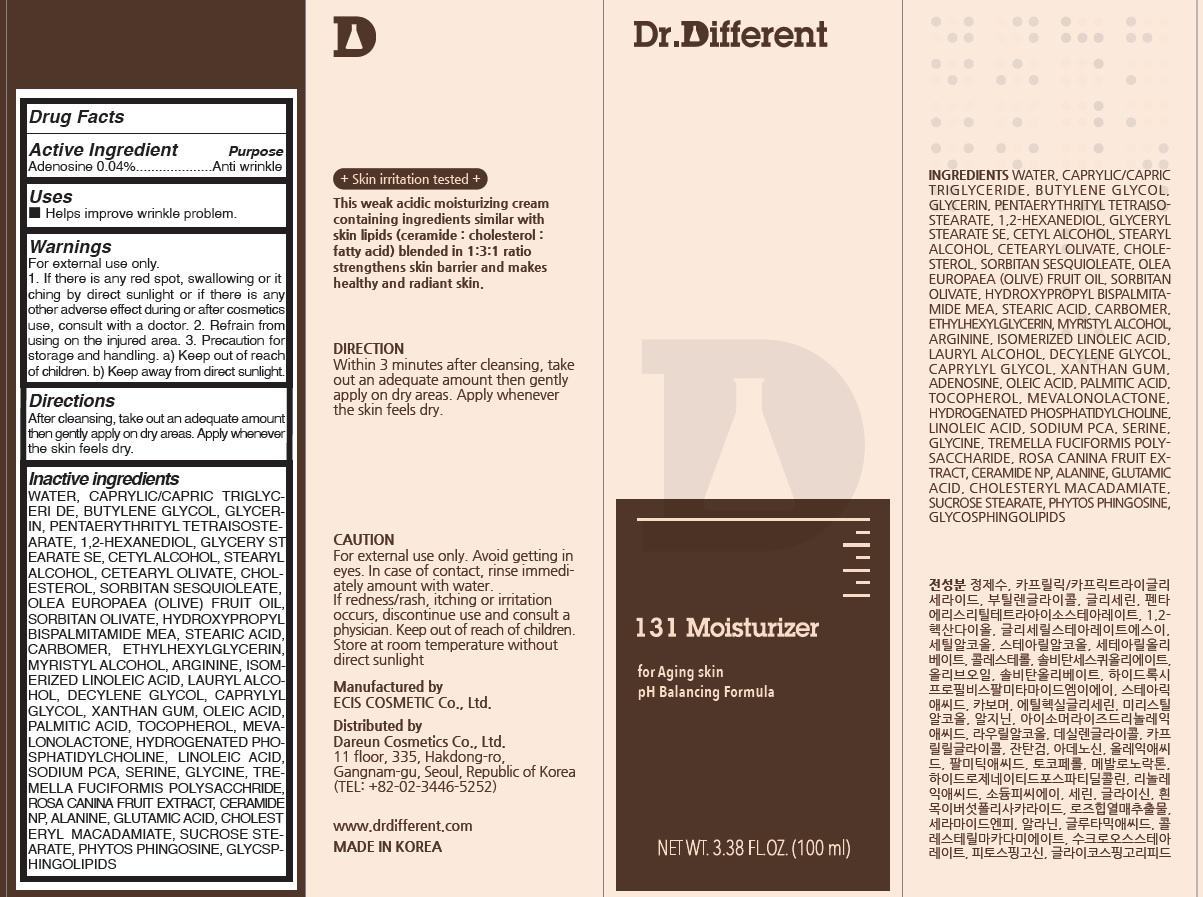 DRUG LABEL: Dr.Different 131 Moisturizer
NDC: 81710-020 | Form: LIQUID
Manufacturer: Dareun Cosmetics Co., Ltd.
Category: otc | Type: HUMAN OTC DRUG LABEL
Date: 20210409

ACTIVE INGREDIENTS: Adenosine 0.04 g/100 mL
INACTIVE INGREDIENTS: WATER; MEDIUM-CHAIN TRIGLYCERIDES; BUTYLENE GLYCOL

ACTIVE INGREDIENT

Adenosine 0.04%

INACTIVE INGREDIENTS

WATER, CAPRYLIC/CAPRIC TRIGLYCERIDE, BUTYLENE GLYCOL, GLYCERIN, PENTAERYTHRITYL TETRAISOSTEARATE, 1,2-HEXANEDIOL, GLYCERYL STEARATE SE, CETYL ALCOHOL, STEARYL ALCOHOL, CETEARYL OLIVATE, CHOLESTEROL, SORBITAN SESQUIOLEATE, OLEA EUROPAEA (OLIVE) FRUIT OIL, SORBITAN OLIVATE, HYDROXYPROPYL BISPALMITAMIDE MEA, STEARIC ACID, CARBOMER, ETHYLHEXYLGLYCERIN, MYRISTYL ALCOHOL, ARGININE, ISOMERIZED LINOLEIC ACID, LAURYL ALCOHOL, DECYLENE GLYCOL, CAPRYLYL GLYCOL, XANTHAN GUM, OLEIC ACID, PALMITIC ACID, TOCOPHEROL, MEVALONOLACTONE, HYDROGENATED PHOSPHATIDYLCHOLINE, LINOLEIC ACID, SODIUM PCA, SERINE, GLYCINE, TREMELLA FUCIFORMIS POLYSACCHARIDE, ROSA CANINA FRUIT EXTRACT, CERAMIDE NP, ALANINE, GLUTAMIC ACID, CHOLESTERYL MACADAMIATE, SUCROSE STEARATE, PHYTOS PHINGOSINE, GLYCOSPHINGOLIPIDS

PURPOSE

Anti wrinkle

WARNINGS

For external use only.
1. If there is any red spot, swallowing or itching by direct sunlight or if there is any other adverse effect during or after cosmetics use, consult with a doctor.
2. Refrain from using on the injured area.
3. Precaution for storage and handling.
a) Keep out of reach of children.
b) Keep away from direct sunlight.

KEEP OUT OF REACH OF CHILDREN

Uses

■ Helps improve wrinkle problem.

Directions

■ After cleansing, take out an adequate amount then gently apply on dry areas. Apply whenever the skin feels dry.